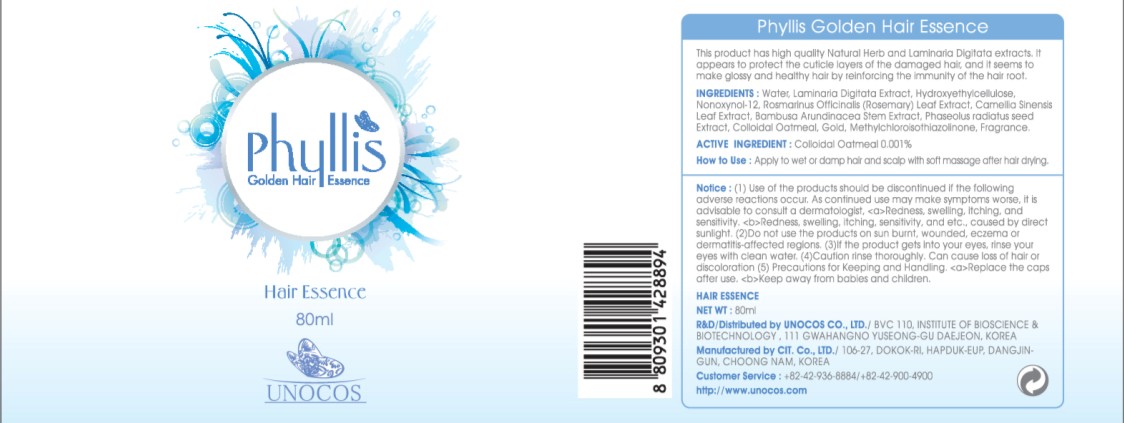 DRUG LABEL: PHYLLIS GOLDEN
NDC: 52841-020 | Form: SOLUTION
Manufacturer: UNOCOS CO., LTD.
Category: otc | Type: HUMAN OTC DRUG LABEL
Date: 20110121

ACTIVE INGREDIENTS: OATMEAL 0.0008 mL/80 mL
INACTIVE INGREDIENTS: WATER; MUNG BEAN; GOLD

Drug Facts

Active Ingredient: OATMEAL

Inactive Ingredients:

WATER, LAMINARIA DIGITATA EXTRACT, HYDROXYETHYLCELLULOSE, NONOXYNOL-12, ROSMARINUS OFFICINALIS (ROSEMARY) LEAF EXTRACT, CAMELLIA SINENSIS LEAF EXTRACT, BAMBUSA ARUNDINACEA STEM EXTRACT, PHASEOLUS RADIATUS SEED EXTRACT, GOLD, METHYLCHLOROISOTHIAZOLINONE, FRAGRANCE

Purpose:

It appears to protect the cuticle layers of the damage hair, and it seems to make glossy and healthy hair by reinforcing the immunity of the hair root.

WARNINGS:

Use of the products should be discontinued if the following adverse reactions occur. As continued use may make symptoms worse, it is advisable to consult a dermatologist, Redness, swelling, itching, and sensitivity.
Redness, swelling, itching, sensitivity, and etc., caused by direct sunlight.
Do not use the products on sun burnt, wounded, eczema or dermatitis-affected regions.
If the product gets into your eyes, rinse your eyes with clean water.
Caution rinse thoroughly. Can cause loss of hair or discoloration.

Keep out of reach of children:
Replace the caps after use.
Keep away from babies and children.

INDICATIONS AND USAGE

How to Use:

Apply to wet or damp hair and scalp with soft massage after hair drying.

Dosage and Administration:

Apply to wet or damp hair and scalp with soft massage after hair drying.